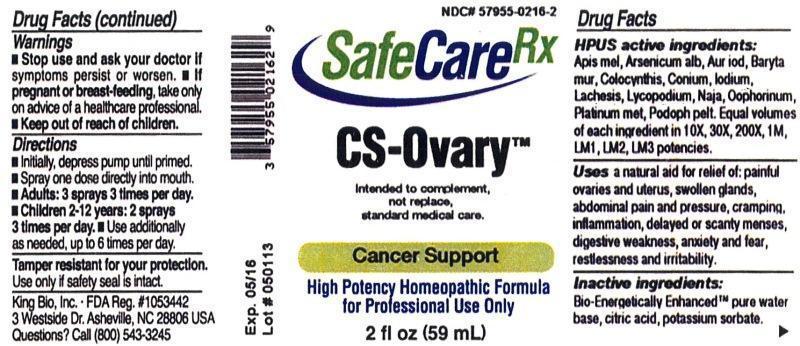 DRUG LABEL: CS-Ovary
NDC: 57955-0216 | Form: LIQUID
Manufacturer: King Bio Inc.
Category: homeopathic | Type: HUMAN OTC DRUG LABEL
Date: 20140113

ACTIVE INGREDIENTS: APIS MELLIFERA 10 [hp_X]/59 mL; ARSENIC TRIOXIDE 10 [hp_X]/59 mL; GOLD MONOIODIDE 10 [hp_X]/59 mL; BARIUM CHLORIDE DIHYDRATE 10 [hp_X]/59 mL; CITRULLUS COLOCYNTHIS FRUIT PULP 10 [hp_X]/59 mL; CONIUM MACULATUM FLOWERING TOP 10 [hp_X]/59 mL; IODINE 10 [hp_X]/59 mL; LACHESIS MUTA VENOM 10 [hp_X]/59 mL; LYCOPODIUM CLAVATUM SPORE 10 [hp_X]/59 mL; NAJA NAJA VENOM 10 [hp_X]/59 mL; SUS SCROFA OVARY 10 [hp_X]/59 mL; PLATINUM 10 [hp_X]/59 mL; PODOPHYLLUM 10 [hp_X]/59 mL
INACTIVE INGREDIENTS: WATER; CITRIC ACID MONOHYDRATE; POTASSIUM SORBATE

Insecurity™

ACTIVE INGREDIENT

HPUS active ingredients: Apis mellifica, Arsenicum album, Aurum iodatum, Baryta muriatica, Colocynthis, Conium maculatum, Iodium, Lachesis mutus, Lycopodium clavatum, Naja tripudians, Oophorinum, Platinum metallicum, Podophyllum peltatum. Equal volumes of each ingredient in 10X, 30X, 200X, 1M, LM1, LM2, LM3 potencies.

INDICATIONS AND USAGE

Uses a natural aid for relief of:painful ovaries and uterus, swollen glands, abdominal pain and pressure, cramping, inflammation, delayed or scanty menses. digestive weakness, anxiety and fear, restlessness and irritability.

INACTIVE INGREDIENT

Inactive Ingredients: Bio-Energetically Enhanced™ pure water, citric acid and potassium sorbate.

Warnings

- Stop use and ask a docter if symptoms persist or worsen.
- If pregnant or breast-feeding, take only on advice of a healthcare professional.

- Keep out of reach of children.

Directions

- Initially, depress pump until primed.
- Spray one dose directly into mouth.
- Adults: 3 sprays 3 times per day.
- Children 2-12 years: 2 sprays 3 times per day.
- Use additionally as needed, up to 6 times per day.

OTHER SAFETY INFORMATION

Tamper resistant for your protection. Use only if safety seal is intact.

PURPOSE

Uses a natural aid for relief of:

- painful ovaries and uterus
- swollen glands
- abdominal pain and pressure
- cramping
- inflammation
- delayed or scanty menses
- digestive weakness
- anxiety and fear
- restlessness and irritability